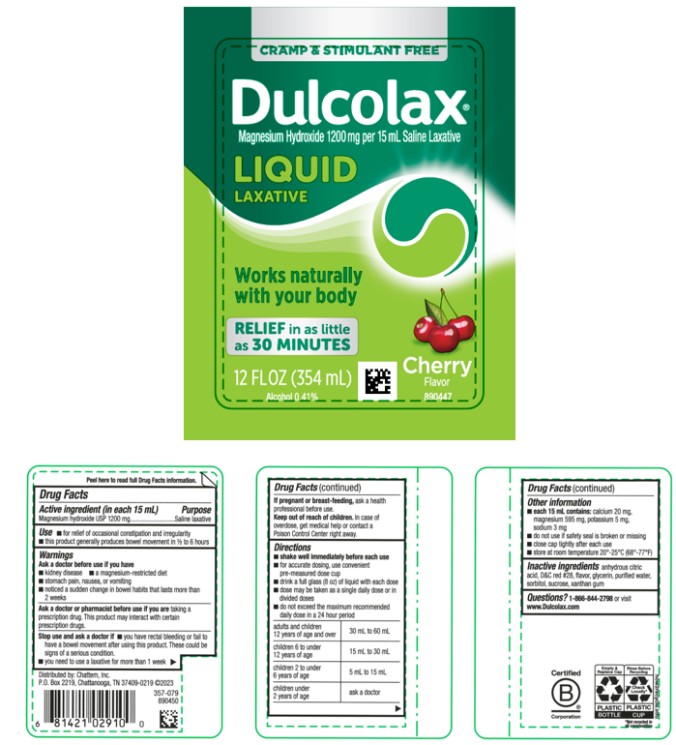 DRUG LABEL: Dulcolax
NDC: 41167-0291 | Form: LIQUID
Manufacturer: Chattem, Inc.
Category: otc | Type: HUMAN OTC DRUG LABEL
Date: 20250211

ACTIVE INGREDIENTS: MAGNESIUM HYDROXIDE 1200 mg/15 mL
INACTIVE INGREDIENTS: ANHYDROUS CITRIC ACID; D&C RED NO. 28; CHERRY; GLYCERIN; WATER; SORBITOL; SUCROSE; XANTHAN GUM

Dulcolax Liquid Laxative Cherry

Dulcolax®

Liquid Saline Laxative – Cherry

Drug Facts

Active ingredient (in each 15 mL)

Magnesium hydroxide 1200 mg

Purpose

Saline laxative

Use

● for relief of occasional constipation and irregularity

● this product generally produces bowel movement in ½ to 6 hours

Warnings

Ask a doctor before use if you have

● kidney disease

● a magnesium-restricted diet

● stomach pain, nausea or vomiting

● noticed a sudden change in bowel habits that lasts more than 2 weeks

Ask a doctor or pharmacist before use if you are

taking a prescription drug. This product may interact with certain prescription drugs.

Stop use and ask a doctor if

● you have rectal bleeding or fail to have a bowel movement after using this product. These could be signs of a serious condition.

● you need to use a laxative for more than 1 week

If pregnant or breast-feeding,

ask a health professional before use.

Keep out of reach of children.

In case of overdose, get medical help or contact a Poison Control Center right away.

Directions

● shake well immediately before each use

● for accurate dosing, use convenient pre-measured dose cup

● drink a full glass (8 oz) of liquid with each dose

● dose may be taken as a single daily dose or in divided doses

● do not exceed the maximum recommended daily dose in a 24 hour period

adults and children 12 years of age and over | 30 mL to 60 mL
children 6 to under 12 years of age | 15 mL to 30 mL
children 2 to under 6 years of age | 5 mL to 15 mL
children under 2 years of age | ask a doctor

Other information

● each 15 mL contains:

calcium 20 mg, magnesium 595 mg, potassium 5 mg, sodium 3 mg

● do not use if safety seal is broken or missing

● close cap tightly after each use

● store at room temperature 20°-25°C (68°-77°F)

Inactive ingredients

anhydrous citric acid, D&C red #28, flavor, glycerin, purified water, sorbitol, sucrose, xanthan gum

Questions?

Call 1-866-844-2798 or visit www.Dulcolax.com

PRINCIPAL DISPLAY PANEL

CRAMP & STIMULANT FREE
Dulcolax
Magnesium Hydroxide 1200 mg per 15 mL Saline Laxative
Liquid
LAXATIVE
Cherry Flavor

12 Fl Oz (354 mL)